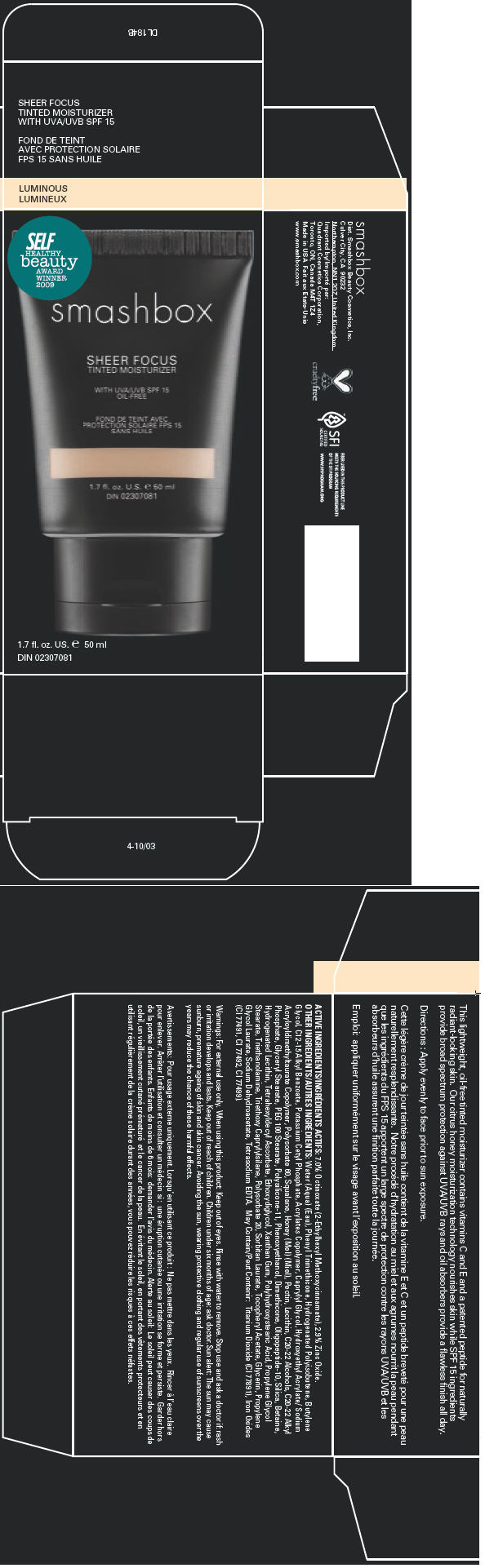 DRUG LABEL: SHEER FOCUS 
NDC: 10348-003 | Form: LIQUID
Manufacturer: SMASHBOX  BEAUTY COSMETICS, INC
Category: otc | Type: HUMAN OTC DRUG LABEL
Date: 20120113

ACTIVE INGREDIENTS: OCTINOXATE 7 mL/100 mL; ZINC OXIDE 2.8 mL/100 mL
INACTIVE INGREDIENTS: Water; Phenyl Trimethicone; Butylene Glycol; Alkyl (C12-15) Benzoate; Potassium Cetyl Phosphate; Caprylyl Glycol; Polysorbate 60; Squalane; Honey; Pectin; C20-22 Alcohols; C20-22 Alkyl Phosphate; Glyceryl Monostearate; Peg-100 Stearate; Phenoxyethanol; Dimethicone; Silicon Dioxide; Betaine; Hydrogenated Soybean Lecithin; Tetrahexyldecyl Ascorbate; Diethylene Glycol Monoethyl Ether; Xanthan Gum; Trolamine; Triethoxycaprylylsilane; Polysorbate 20; Sorbitan Monolaurate; Alpha-Tocopherol Acetate; Glycerin; Sodium Dehydroacetate; Edetate Sodium; Ferric Oxide Red; Ferric Oxide Yellow; Ferrosoferric Oxide; Titanium Dioxide

SHEER FOCUS
TINTED MOISTURIZER

Directions

Apply evenly to face prior to sun exposure.

ACTIVE INGREDIENTS

7.0% Octinoxate (2-Ethylhexyl Methoxycinnamate), 2.9% Zinc Oxide.

OTHER INGREDIENTS

Water (Aqua) (Eau), Phenyl Trimethicone, Hydrogenated Polyisobutene, Butylene Glycol, C12-15 Alkyl Benzoate, Potassium Cetyl Phosphate, Acrylates Copolymer, Caprylyl Glycol, Hydroxyethyl Acrylate/ Sodium Acryloyldimethyltaurate Copolymer, Polysorbate 60, Squalane, Honey (Mel) (Miel), Pectin, Lecithin, C20-22 Alcohols, C20-22 Alkyl Phosphate, Glyceryl Stearate, PEG 100 Stearate, Polysilicone-11, Phenoxyethanol, Dimethicone, Oligopeptide-10, Silica, Betaine, Hydrogenated Lecithin, Tetrahexyldecyl Ascorbate, Ethoxydiglycol, Xanthan Gum, Polyhydroxystearic Acid, Propylene Glycol Stearate, Triethanolamine, Triethoxy Caprylylsilane, Polysorbate 20, Sorbitan Laurate, Tocopheryl Acetate, Glycerin, Propylene Glycol Laurate, Sodium Dehydroacetate, Tetrasodium EDTA. May Contain/Peut Contenir: Titanium Dioxide (CI 77891), Iron Oxides (CI 77491, CI 77492, CI 77499).

Warnings

For external use only.

When using this product: Keep out of eyes. Rinse with water to remove.

STOP USE

Stop use and ask a doctor if: rash or irritation develops and lasts.

Keep out of reach of children. Children under six months of age: ask doctor.

Sun alert: The sun may cause sunburn, premature ageing of skin and skin cancer. Avoiding the sun, wearing protective clothing and regular use of sunscreens over the years may reduce the chance of these harmful effects.

Dist. Smashbox Beauty Cosmetics, Inc.
Culver City, CA 90232
Northampton, NN1 2QZ,United Kingdom

PRINCIPAL DISPLAY PANEL - 50 ml Carton

SELF
HEALTHY
beauty
AWARD
WINNER
2009

smashbox

SHEER FOCUS
TINTED MOISTURIZER

WITH UVA/UVB SPF 15
OIL-FREE

1.7 fl. oz. US. e 50 ml
DIN 02307081